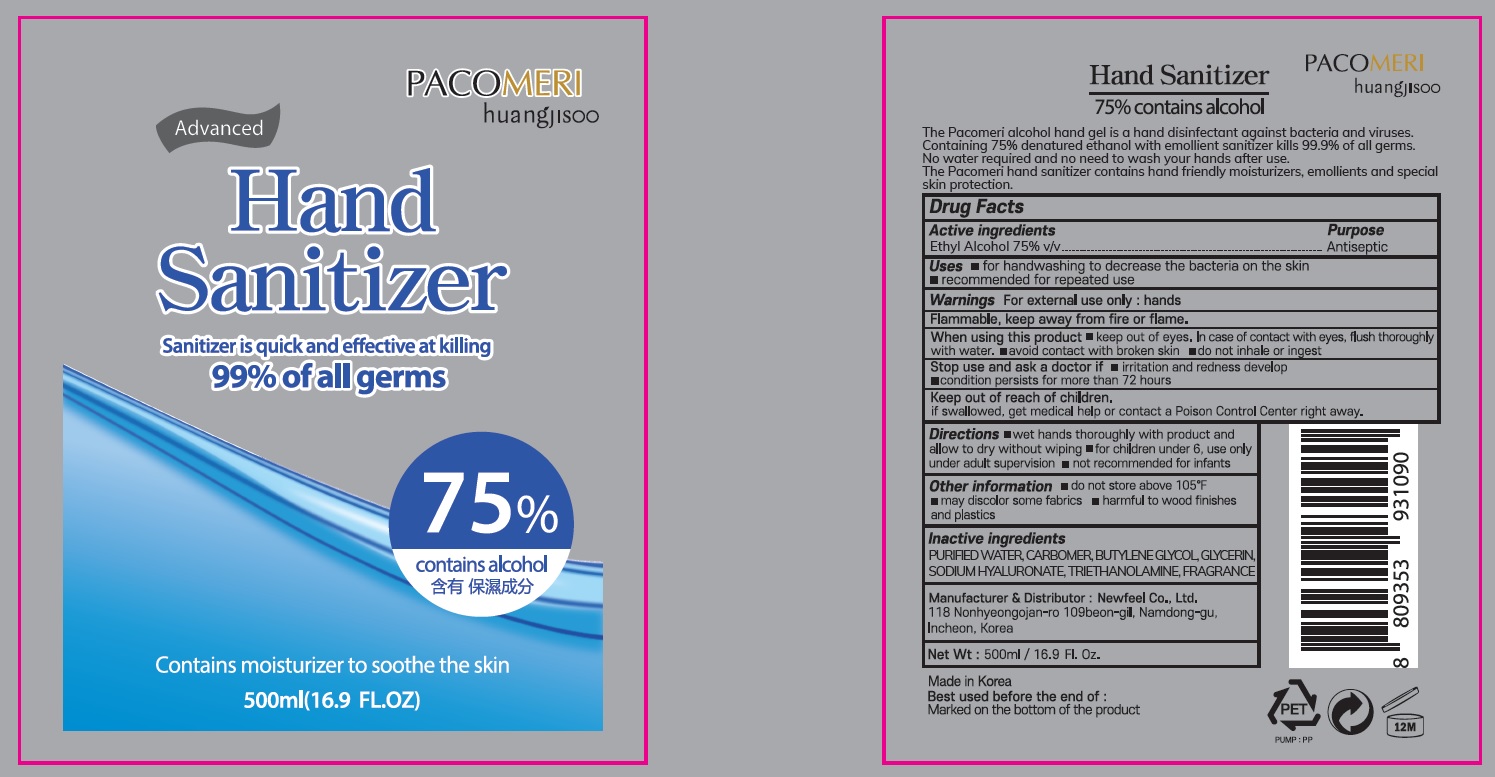 DRUG LABEL: Pacomeri Advanced Hand Sanitizer
NDC: 73713-060 | Form: GEL
Manufacturer: Newfeel
Category: otc | Type: HUMAN OTC DRUG LABEL
Date: 20200501

ACTIVE INGREDIENTS: ALCOHOL 375 mL/500 mL
INACTIVE INGREDIENTS: Water; CARBOMER HOMOPOLYMER, UNSPECIFIED TYPE; BUTYLENE GLYCOL; Glycerin; HYALURONATE SODIUM; TROLAMINE

ACTIVE INGREDIENT

Active ingredients: Ethyl alcohol 75% v/v

INACTIVE INGREDIENT

Inactive ingredients:

PURIFIED WATER, CARBOMER, BUTYLENE GLYCOL, GLYCERIN, SODIUM HYALURONATE, TRIETHANOLAMINE, FRAGRANCE

PURPOSE

Purpose: Antiseptic

WARNINGS

For external use only : hands
Flammable, keep away from fire or flame.
When using this product ■ keep out of eyes. In case of contact with eyes, flush thoroughly with water. ■ avoid contact with broken skin. ■ do not inhale or ingest
Stop use and ask a doctor if ■irritation and redness develop ■ condition persists for more than 72 hours
Keep out of reach of children.
If swallowed, get medical help or contact a Poison Control Center right away.

KEEP OUT OF REACH OF CHILDREN

If swallowed, get medical help or contact a Poison Control Center right away.

Uses

■ for handwashing to decrease the bacteria on the skin
■ recommended for repeated use

Directions

■ wet hands thoroughly with product and allow to dry without wiping

■ for children under 6, use only under adult supervision

■ not recommended for infants

Other information

■ do not store above 105℉

■ may discolor some fabrics

■ harmful to wood finishes and plastics